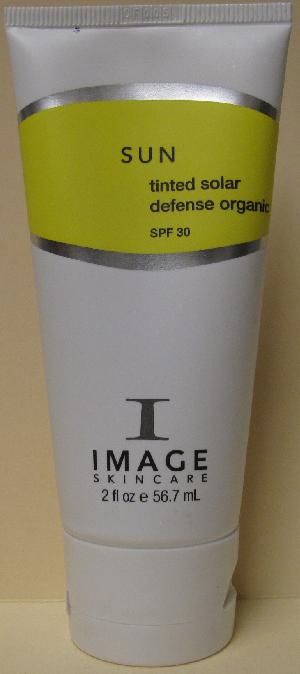 DRUG LABEL: SUN Tinted Solar Defense Organic SPF 30
NDC: 62742-4041 | Form: CREAM
Manufacturer: Allure Labs, Inc.
Category: otc | Type: HUMAN OTC DRUG LABEL
Date: 20100702

ACTIVE INGREDIENTS: ZINC OXIDE 170 mg/1 mL

Drug Facts

Purpose:

A physical organic UVA/UVB broad spectrum daily moisturizer. Provides an even skin tone and healthy glow. Ultimate protection against the aging effects of the sun and other environmental pollutants. Enriched with essential vitamins and anti-oxidants that prevent free facical damage. Preserves skin hydration for the entire day.

Paraben Free

Provides Healthy even glow

Excellent for sensitive skin

Chemical free

Water resistant

Directions:

Apply liberally 15-30 minutes prior to sun exposure or as needed for a even skin tone. Reapply regulary or after prolonged swimming or activity.

Indications:

Sensitive skin, Sun exposure, uneven skin tone

Active Ingredients:

Zinc Oxide 17%

Inactive Ingredients:

Water (Aqua), Butylene Glycol, Glycerin, Caprylic/Capric Triglyceride, Glyceryl Stearate, PEG 100 Stearate, Sorbitan Stearate, Imperata Cylindrica Root Extract, Phenoxyethanol, Tocophery Linoleate, Ascorbyl Palmitate (Vitamin C), Lecithin, Tocopherol (Vitamin E), Xanthan Gum, Citric Acid, C13-14 Isoparaffin, PEG 8, Ethylhexylglycerin, Sodium Lactate, Micrococcus Lysate, Arabidopsis Extract, Plankton Extract, Teprenone, Phoenix dactylifera (date) Extract, Laureth-7, Disodium EDTA, Dipotassium Glycyrrizate, Caprylyl Glycol, Ascorbic Acid (Viamin C), Carbomer, Iron Oxides (CL 72124, Cl 7212 and Cl72123)

PACKAGE LABEL

Distributor:

Image International

Palm Beach, FL 33411 USA

Image of the Product:

SUN Tinted Solar Defense Organic SPF 30